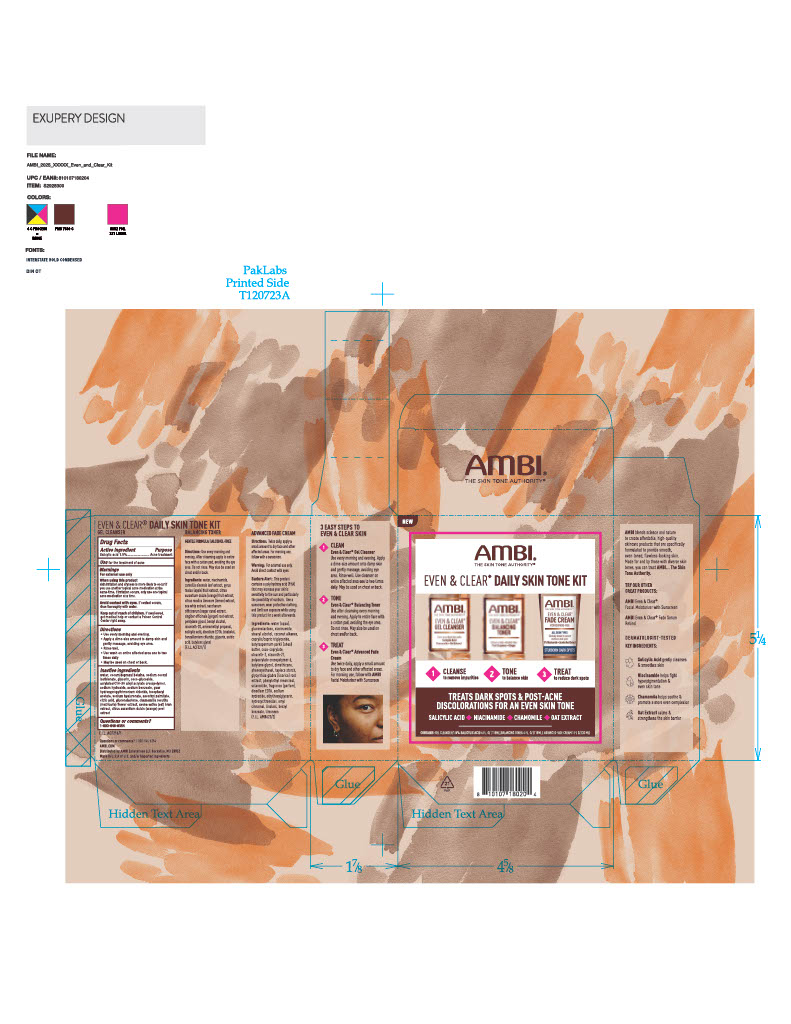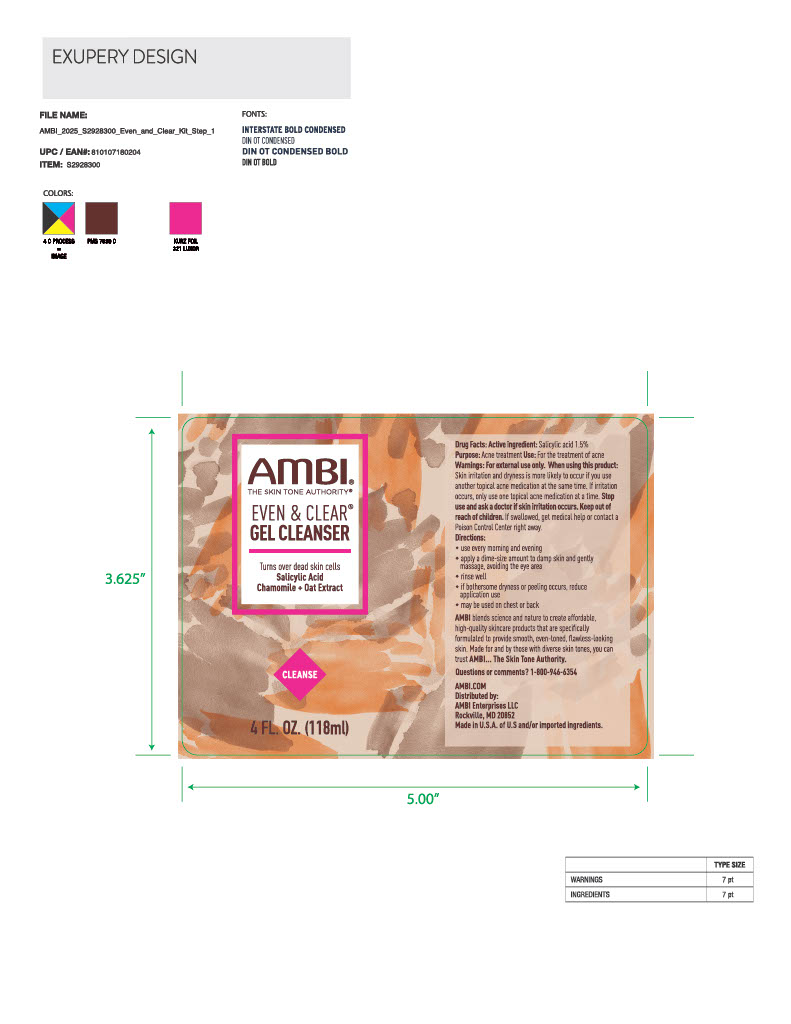 DRUG LABEL: Ambi Even and Clean Skin Tone Kit
NDC: 73453-110 | Form: KIT | Route: TOPICAL
Manufacturer: Ambi Enterprise LLC
Category: otc | Type: HUMAN OTC DRUG LABEL
Date: 20251218

ACTIVE INGREDIENTS: SALICYLIC ACID 15 mg/1 mL
INACTIVE INGREDIENTS: COCAMIDOPROPYL BETAINE; GLYCERIN; SODIUM BENZOATE; GUAR HYDROXYPROPYLTRIMONIUM CHLORIDE; CITRIC ACID; CHAMOMILE; SODIUM COCOYL ISETHIONATE; GLUCONOLACTONE; COCO-GLUCOSIDE; SODIUM HYALURONATE; ASCORBYL PALMITATE; .ALPHA.-TOCOPHEROL ACETATE; ACRYLATES/C10-30 ALKYL ACRYLATE CROSSPOLYMER (60000 MPA.S); SODIUM HYDROXIDE; AVENA SATIVA (OAT) BRAN; CITRUS AURANTIUM DULCIS (ORANGE) OIL; WATER

Ambi Even and Clear Skin Tone Kit

Active Ingredient

Salicylic acid 1.5%

Purpose

Acne treatment

Use

For the treatment of acne

Warnings

For external use only

When using this product

Skin irritation and dryness is more likely to occur if you use another topical acne medication at the same time. If irritation occurs, only use one topical acne medication at a time.

Avoid contact with eyes. If contact occurs, rinse thoroughly with water.

Keep out of reach of children

If swallowed, get medical help or contact a Poison Control Center right away

Directions

Use every morning and evening

Apply a dime-size amount to damp skin and gently massage, avoiding eye area

Rinse well

Use wash on entire affected area one to two times daily

May be used on chest and back

Inactive ingredients

water, cocamidopropyl betaine, sodium cocoyl isethionate, glycerin, coco-glucoside, acrylates/C10-30 alkyl acrylate crosspolymer, sodium hydroxide, sodium benzoate, guar hydroxypropyltrimonium chloride, tocopheryl acetate, sodium hyaluronate, ascorbyl palmitate, citric acid, gluconolactone, chamomilla recutita (matricaria) flower extract, avena sativa (oat) bran extract, citrus aurantium dulcis (orange) peel extract

Questions or comments?

1-800-946-6354